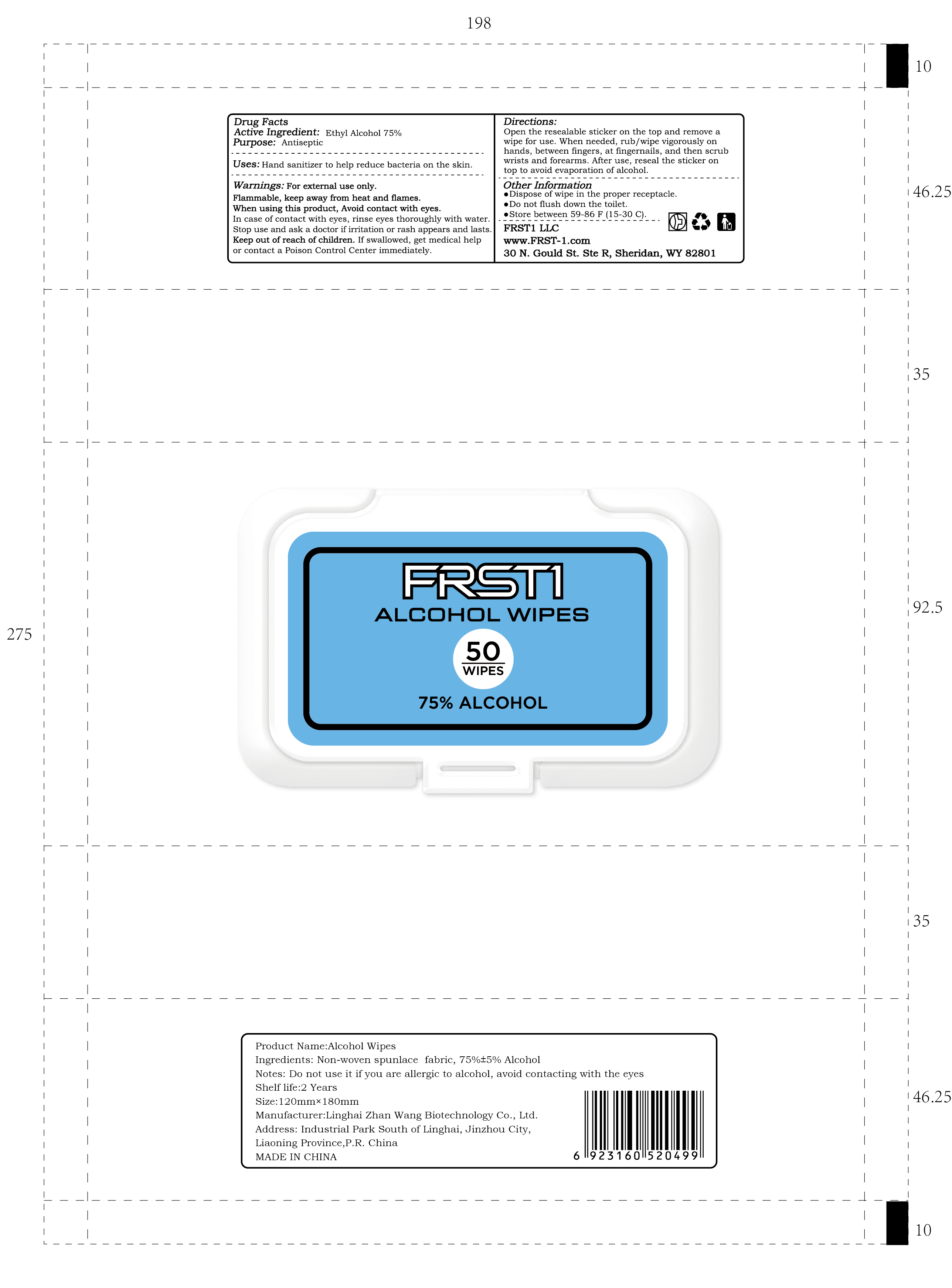 DRUG LABEL: FRST1 ALCOHOL WIPES
NDC: 75269-007 | Form: CLOTH
Manufacturer: LINGHAI ZHANWANG BIOTECHNOLOGY CO.,LTD.
Category: otc | Type: HUMAN OTC DRUG LABEL
Date: 20231024

ACTIVE INGREDIENTS: ALCOHOL 75 mL/100 mL
INACTIVE INGREDIENTS: WATER

75269-007 FRST1 ALCOHOL WIPES

Active Ingredient

Ethyl Alcohol 75%

Purpose

Antiseptic

Uses

Hand sanitizer to help reduce bacteria on the skin.

Warnings

For external use only.

Flammable, keep away from heat and flames.

When using this product, Avoid contact with eyes.

In case of contact with eyes, rinse eyes thoroughly with water.

Stop use and ask a doctor if irritation or rash appears and lasts.

Keep out of reach of children. If swallowed, get medical help or contact a Poison Control Center immediately.

When using this product, Avoid contact with eyes.

In case of contact with eyes, rinse eyes thoroughly with water.

Stop use and ask a doctor if irritation or rash appears and lasts.

Keep out of reach of children. If swallowed, get medical help or contact a Poison Control Center immediately.

Directions

Open the resealable sticker on the top and remove a wipe for use. When needed, rub/wipe vigorously on hands, between fingers, at fingernails, and then scrub wrists and forearms. After use, reseal the sticker on top to avoid evaporation of alcohol.

Other Information

•Dispose of wipe in the proper receptacle.

•Do not flush down the toilet.

•Store between 59-86 F (15-30 C).

Inactive Ingredient

Water

PACKAGE LABEL

50 WIPES, NDC: 75269-007-01